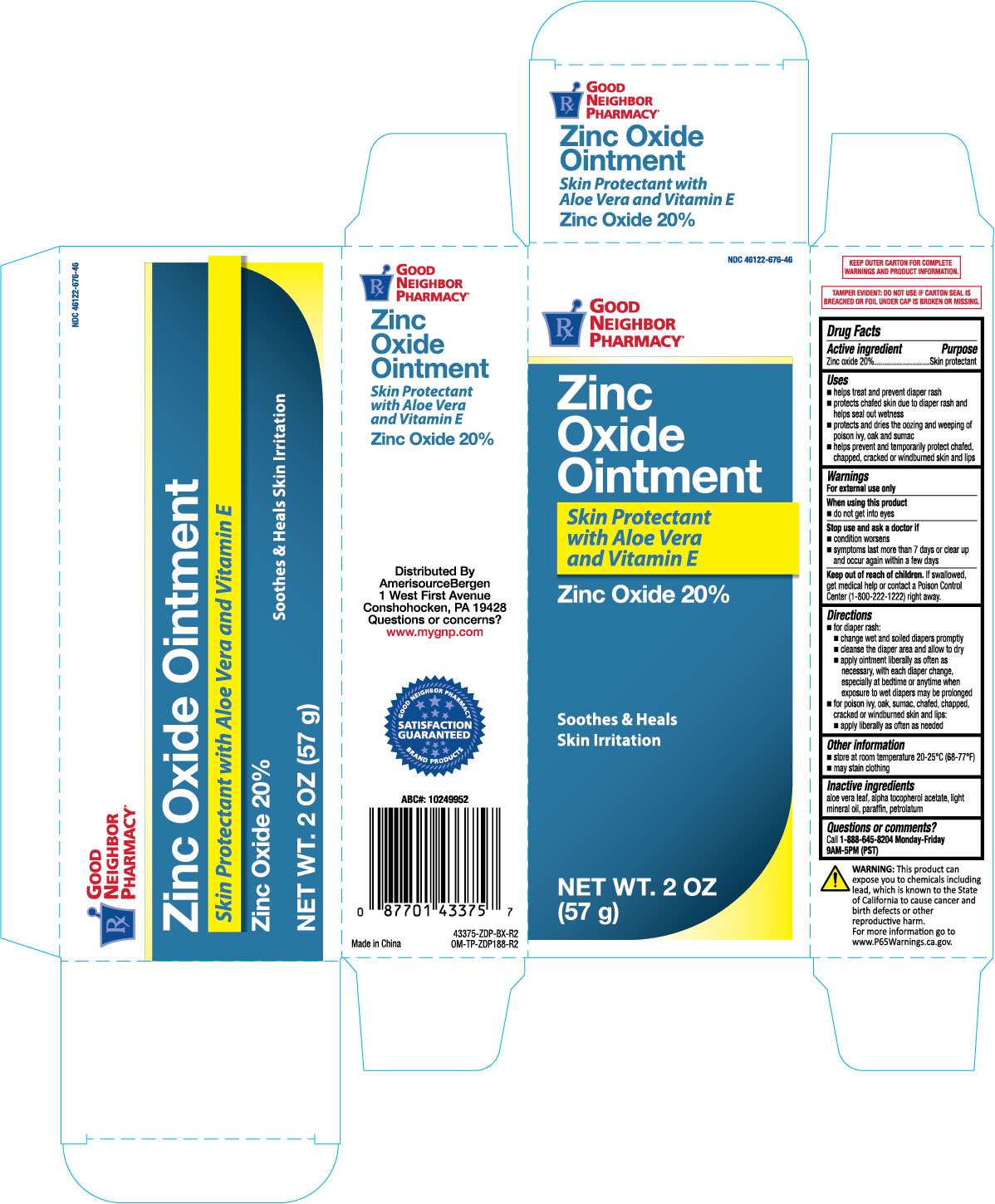 DRUG LABEL: Good Neighbor Pharmacy Skin Protectant
NDC: 46122-676 | Form: OINTMENT
Manufacturer: AMERISOURCE BERGEN
Category: otc | Type: HUMAN OTC DRUG LABEL
Date: 20251029

ACTIVE INGREDIENTS: ZINC OXIDE 0.2 g/1 g
INACTIVE INGREDIENTS: ALOE VERA LEAF; PARAFFIN; .ALPHA.-TOCOPHEROL ACETATE; LIGHT MINERAL OIL; PETROLATUM

GNP Zinc Oxide Ointment 2 oz. 43375 ZDP

Active ingredient Purpose

Zinc oxide 20%...............................................Skin protectant

Uses

- helps treat and prevent diaper rash
- protects chafed skin due to diaper rash and helps seal out wetness
- protects and dries the oozing and weeping of poison ivy, oak and sumac
- helps prevent and temporarily protect chafed, chapped, cracked, or windburned skin and lips

Warnings

For external use only

When using this product

- do not get into eyes

Stop use and ask a doctor if

- condition worsens
- symptoms last more than 7 days or clear up and occur again within a few days

Keep out of reach of children. If swallowed, get medical help or contact a Poison Control Center (1-800-222-1222) right away.

Directions

- for diaper rash:
- change wet and soiled diapers promptly
- cleanse the diaper area and allow to dry
- apply ointment liberally as often as necessary, with each diaper change, especially at bedtime or anytime when exposure to wet diapers may be prolonged
- for poison ivy, oak, sumac, chafed, chapped, cracked or windburned skin and lips:
- apply liberally as often as needed

Other information

- store at room temperature 20-25°C (68-77°F)
- may stain clothing

INACTIVE INGREDIENT

Inactive ingredients .alpha.-tocopherol acetate, aloe vera leaf, light mineral oil, praffin, petrolatum

DOSAGE AND ADMINISTRATION

Distributed by:

Amerisource Bergen

1300 Morris Drive

Chesterbrook, PA 19087

Made in China